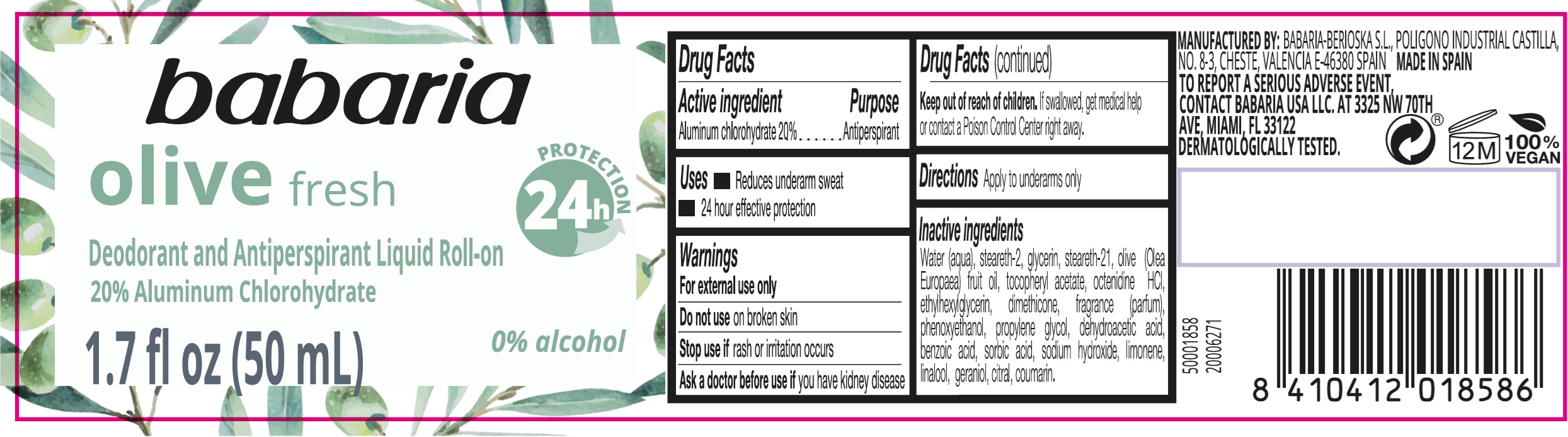 DRUG LABEL: Babaria Olive Fresh Deodorant and Antiperspirant Liquid Roll-On
NDC: 78283-006 | Form: EMULSION
Manufacturer: BERIOSKA SL
Category: otc | Type: HUMAN OTC DRUG LABEL
Date: 20251220

ACTIVE INGREDIENTS: ALUMINUM CHLOROHYDRATE 200 mg/1 mL
INACTIVE INGREDIENTS: WATER; STEARETH-2; GLYCERIN; STEARETH-21; OLIVE OIL; .ALPHA.-TOCOPHEROL ACETATE; OCTENIDINE HYDROCHLORIDE; ETHYLHEXYLGLYCERIN; DIMETHICONE; PHENOXYETHANOL; PROPYLENE GLYCOL; DEHYDROACETIC ACID; BENZOIC ACID; SORBIC ACID; SODIUM HYDROXIDE; LIMONENE, (+)-; LINALOOL, (+/-)-; GERANIOL; CITRAL; COUMARIN

Babaria Olive Fresh Deodorant and Antiperspirant Liquid Roll-On

Active ingredient

Aluminum chlorohydrate 20%

Purpose

Antiperspirant

Uses

• Reduces underarm sweat • 24 hour effective protection

Warnings

For external use only

Do not use

on broken skin

Stop use if

if rash or irritation occurs

Ask a doctor before use if

you have kidney disease

Keep out of reach of children.

If swallowed, get medical help or contact a Posion Control Center right away.

Directions

Apply to underarms only

Inactive ingredients

Water (aqua), steareth-2, glycerin, steareth-21, olive (Olea Europaea) fruit oil, tocopheryl acetate, octenidine HCL, ethylhexylglycerin, dimethicone, fragrance (parfum), phenoxyethanol, propylene glycol, dehydroacetic acid, benzoic acid, sorbic acid sodium hydroxide, limonene, linalool, geraniol, citral, coumarin.